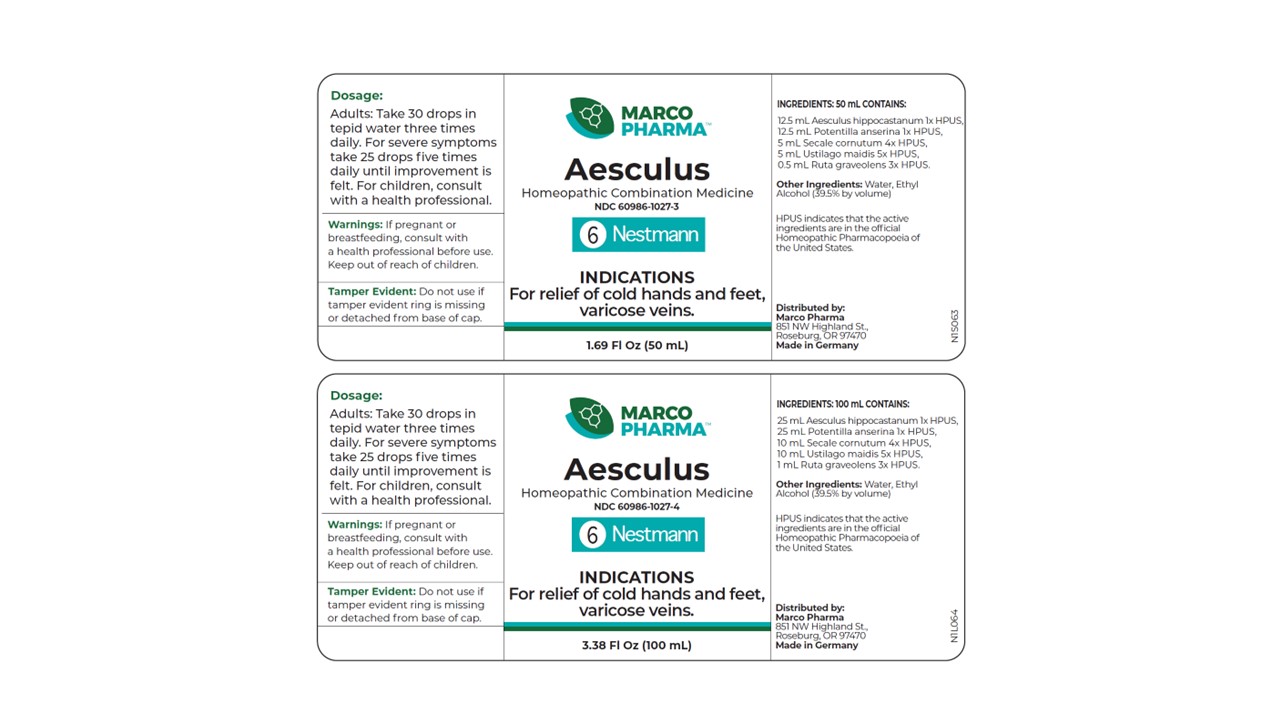 DRUG LABEL: Aesculus
NDC: 60986-1027 | Form: LIQUID
Manufacturer: Marco Pharma International LLC.
Category: homeopathic | Type: HUMAN OTC DRUG LABEL
Date: 20260112

ACTIVE INGREDIENTS: ARGENTINA ANSERINA FLOWERING TOP 1 [hp_X]/1 mL; HORSE CHESTNUT 1 [hp_X]/1 mL; USTILAGO MAYDIS 5 [hp_X]/1 mL; CLAVICEPS PURPUREA SCLEROTIUM 4 [hp_X]/1 mL; RUTA GRAVEOLENS WHOLE 3 [hp_X]/1 mL
INACTIVE INGREDIENTS: ALCOHOL; WATER

Drug Facts

Active Ingredients

Silverweed 1xHPUS

Horse chestnut 1xHPUS

Maize smut 5xHPUS

Rye ergot 4xHPUS

Common rue 3xHPUS

The letters HPUS indicates that the components in this product are officially monographed in the Homeopathic Pharmacopoeia of United Sates.

Purpose

Relief of cold hands and feet; varicose veins.

Keep out of reach of children.

Suggested use

Adults: take 25 drops in tepid water three times daily. For severe symptoms take 20 drops five times daily until improvement is felt. Children receive 1/2 or less of the adult amount.

Warnings

If pregnant or breast-feeding, consult a health professional before use.

DOSAGE AND ADMINISTRATION

(Read Suggested Use Section)

Inactive Ingredients

Ethyl Alcohol (38.5% by vol.) and Water